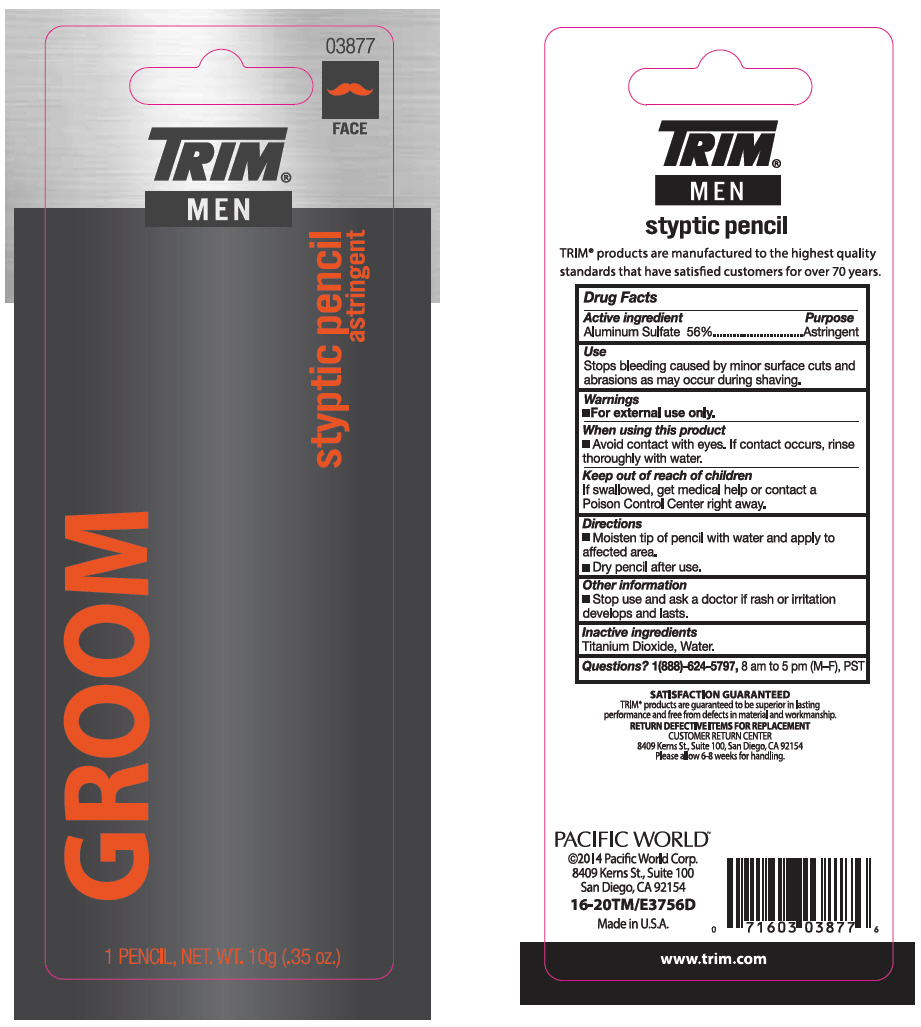 DRUG LABEL: Trim Men Styptic Pencil
NDC: 60193-500 | Form: STICK
Manufacturer: Pacific World Corporation
Category: otc | Type: HUMAN OTC DRUG LABEL
Date: 20141030

ACTIVE INGREDIENTS: Aluminum sulfate 5.6 g/10 g
INACTIVE INGREDIENTS: Titanium dioxide; Water

Trim® Men Styptic Pencil

Drug Facts

Active ingredient

Aluminum Sulfate 56%

Purpose

Astringent

Use

Stops bleeding caused by minor surface cuts and abrasions as may occur during shaving.

Warnings

- For external use only.

When using this product

- Avoid contact with eyes. If contact occurs, rinse thoroughly with water.

Keep out of reach of children

If swallowed, get medical help or contact a Poison Control Center right away.

Directions

- Moisten tip of pencil with water and apply to affected area.
- Dry pencil after use.

Other information

- Stop use and ask a doctor if rash or irritation develops and lasts.

Inactive ingredients

Titanium Dioxide, Water.

Questions?

1(888)-624-5797, 8 am to 5 pm (M–F), PST

PRINCIPAL DISPLAY PANEL - 10 g Cylinder Blister Pack

03877

FACE

TRIM®
MEN

styptic pencil
astringent

GROOM

1 PENCIL, NET. WT. 10g (.35 oz.)